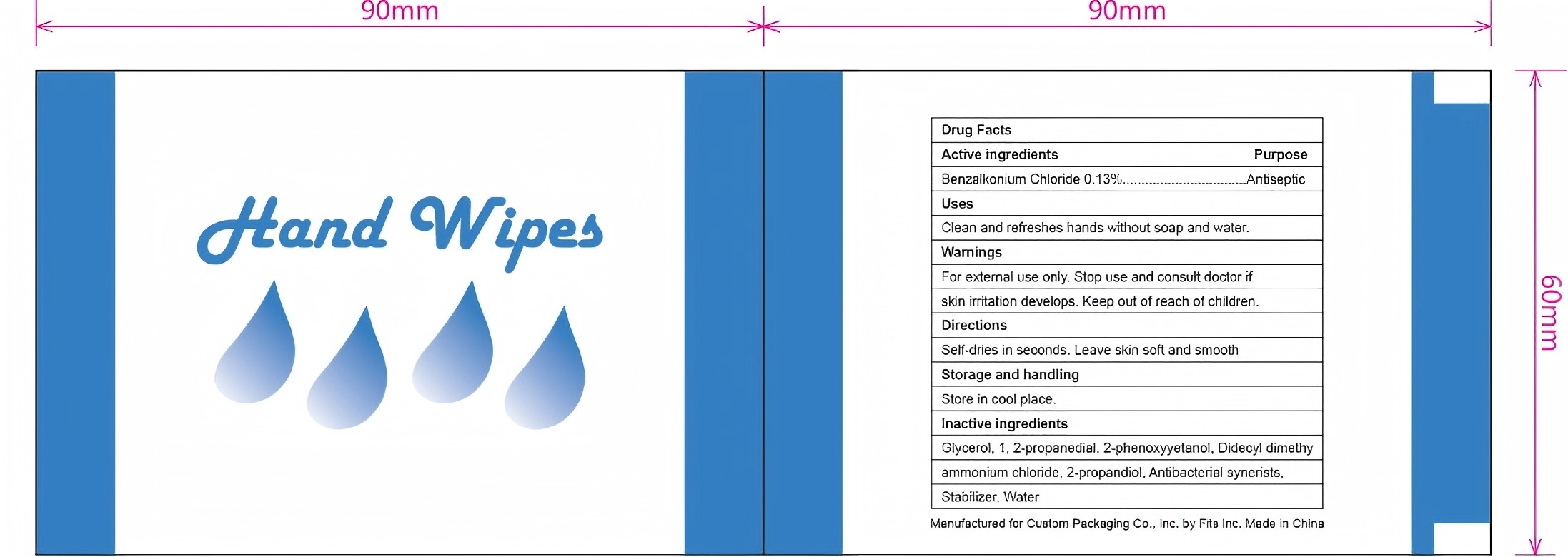 DRUG LABEL: Hand wipes
NDC: 84449-008 | Form: PATCH
Manufacturer: SHENZHEN BENLIJU BIO-TECH CO.,LTD
Category: otc | Type: HUMAN OTC DRUG LABEL
Date: 20260105

ACTIVE INGREDIENTS: BENZALKONIUM CHLORIDE 0.005 g/3.6 g
INACTIVE INGREDIENTS: 1,2,3-PROPANETRIOL, 2-(4-AMINOBENZOATE) 0.018 g/3.6 g; PHENOXYETHANOL 0.0036 g/3.6 g; 3-ISOPROPYLAMINO-1,2-PROPANEDIOL 0.0036 g/3.6 g; WATER 3.5554 g/3.6 g

ACTIVE INGREDIENT

Benzalkonium Chloride

PURPOSE

Clean and refreshes hands without soap and water.

INDICATIONS AND USAGE

Clean and refreshes hands without soap and water.

WARNINGS

For external use only, Stop use and consult doctor if skin irritation develops.

When using this product do not use in ornear the eyes.In case of contact, rinse eyes thoroughly with water.

When using this product keep out of eyes.

STOP USE

For external use only, Stop use and consult doctor if skin irritation develops.

Keep out of reach of children.

DOSAGE AND ADMINISTRATION

Directions: Tear open, unfold and apply to hands.

STORAGE AND HANDLING

Store in cool place.

INACTIVE INGREDIENT

Deionized water, Glycerol, 1,2-propanediol, 2-phenoxyetanol, Didecyl dimethyl ammonium chloride, 2-propandiol, Antibacterial synerists, Stabilizer.